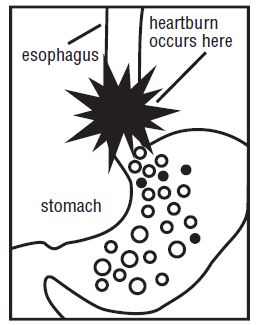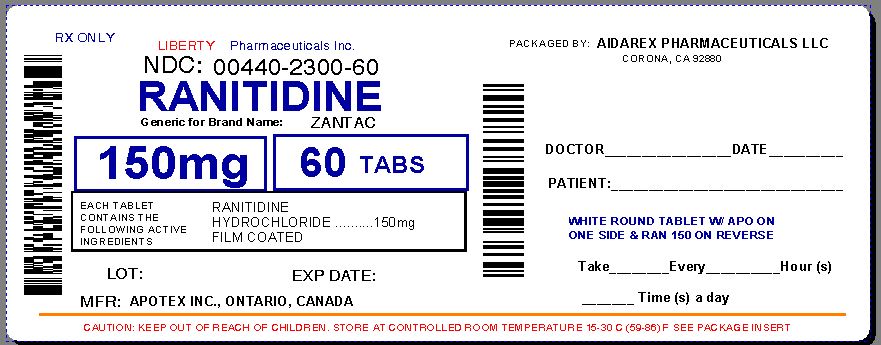 DRUG LABEL: Ranitidine
NDC: 0440-2300 | Form: TABLET, FILM COATED
Manufacturer: Liberty Pharmaceuticals, Inc.
Category: otc | Type: HUMAN OTC DRUG LABEL
Date: 20130924

ACTIVE INGREDIENTS: RANITIDINE HYDROCHLORIDE 150 mg/1 1
INACTIVE INGREDIENTS: CARNAUBA WAX; SILICON DIOXIDE; HYPROMELLOSES; MAGNESIUM STEARATE; CELLULOSE, MICROCRYSTALLINE; POLYDEXTROSE; TITANIUM DIOXIDE; VANILLIN; FERRIC OXIDE RED; FERRIC OXIDE YELLOW

Drug Facts

Active Ingredient(s)

Ranitidine 150 mg (as ranitidine hydrochloride 168 mg)

Purpose

Acid reducer

Use(s)

- Relieves heartburn associated with acid indigestion and sour stomach
- Prevents heartburn associated with acid indigestion and sour stomach brought on by certain foods and beverages

Warnings

Allergy alert: Do not use if you are allergic to ranitidine or any other acid reducers.

Do not use

- with other acid reducers
- if you have kidney disease, except under the advice and supervision of a doctor
- if you have trouble or pain swallowing food, vomiting with blood, or bloody or black stools. These may be signs of a serious condition. See your doctor

Ask a doctor before use if you have

- nausea or vomiting
- stomach pain
- unexplained weight loss
- frequent chest pain
- frequent wheezing, particularly with heartburn
- had heartburn over 3 months. This may be a sign of a more serious condition.
- heartburn with lightheadedness, sweating or dizziness
- chest pain or shoulder pain with shortness of breath; sweating; pain spreading to arms, neck or shoulders; or lightheadedness

Stop use and ask a doctor if

- your heartburn continues or worsens
- you need to take this product for more than 14 days

Pregnancy/Breastfeeding

If pregnant or breastfeeding, ask a health professional before use.

Keep out of reach of children.

In case of overdose, get medical help or contact a Poison Control Center right away.

Directions

Adults and Children 12 years and over:

- to relieve symptoms, swallow 1 tablet with a glass of water
- to prevent symptoms, swallow 1 tablet with a glass of water 30 to 60 minutes before eating food or drinking beverages that cause heartburn
- can be used up to twice daily (do not take more than 2 tablets in 24 hours)
- do not chew tablet
- children under 12 years: ask a doctor

Other Information

- do not use if bottle seal is open or torn
- store at 20° to 25°C (68° to 77°F)
- protect from light
- this product is sodium and sugar free

Inactive Ingredients

carnauba wax, colloidal silicon dioxide, hypromellose, magnesium stearate, microcrystalline cellulose, polydextrose, titanium dioxide, vanillin, red and yellow ferric oxide.

Questions or Comments?

Call 1-800-706-5575 (Monday to Friday 8:30 a.m. – 5:00 p.m. Eastern Standard Time)

Consumer Information

What you should know about

MAXIMUM STRENGTH

Ranitidine Tablets USP, 150 mg / Acid Reducer

(Please read all this information before taking MAXIMUM STRENGTH Ranitidine Tablets USP, 150 mg. Save this leaflet for future reference)

What are MAXIMUM STRENGTH Ranitidine Tablets USP, 150 mg?

MAXIMUM STRENGTH Ranitidine Tablets USP, 150 mg contains 150 mg of ranitidine (as ranitidine hydrochloride, 168 mg), a medicine that doctors have prescribed more than 200 million times worldwide.

What symptoms do MAXIMUM STRENGTH Ranitidine Tablets USP, 150 mg treat and prevent?

MAXIMUM STRENGTH Ranitidine Tablets USP, 150 mg relieves and prevents heartburn associated with acid indigestion and sour stomach.

Certain foods or beverages, and even lying down to sleep, can cause heartburn associated with acid indigestion and sour stomach. It is normal for the stomach to produce acid, especially after consuming food or beverages. However, acid in the wrong place, such as the esophagus, or too much acid, can cause burning pain and discomfort.

Excellent Safety Record

- The ingredient in MAXIMUM STRENGTH Ranitidine Tablets USP, 150 mg, ranitidine, has been prescribed by doctors for years to treat millions of patients safely and effectively. The active ingredient in MAXIMUM STRENGTH Ranitidine Tablets USP, 150 mg has been taken safely with many frequently prescribed medications.
- MAXIMUM STRENGTH Ranitidine Tablets USP, 150 mg are sodium and sugar free.

How should I take MAXIMUM STRENGTH Ranitidine Tablets USP, 150 mg?

- To relieve symptoms, swallow 1 tablet with a glass of water.
- To prevent symptoms, swallow 1 tablet with a glass of water 30 to 60 minutes before eating food or drinking beverages that cause heartburn.

This medicine can be used up to twice daily (do not take more than 2 tablets in 24 hours).

MAXIMUM STRENGTH Ranitidine Tablets USP, 150 mg should not be given to children under 12 years old unless directed by a doctor.

How do MAXIMUM STRENGTH Ranitidine Tablets USP, 150 mg work?

MAXIMUM STRENGTH Ranitidine Tablets USP, 150 mg reduces the production of stomach acid. This is what makes MAXIMUM STRENGTH Ranitidine Tablets USP, 150 mg different from antacids, which neutralize the acid already in your stomach. Antacids do not reduce the production of acid.

Tips for managing heartburn

- Do not lie flat or bend over soon after eating
- Do not eat late at night, or just before bedtime
- Certain foods or drinks are more likely to cause heartburn, such as rich, spicy, fatty, and fried foods, chocolate, caffeine, alcohol, even some fruits and vegetables
- Eat slowly and do not eat big meals
- If you are overweight, lose weight
- If you smoke, quit smoking
- Raise the head of your bed
- Wear loose fitting clothing around your stomach
- Allergy alert: Do not use if you are allergic to ranitidine or other acid reducers

When should I see a doctor?

- Do not use
  - with other acid reducers
  - if you have kidney disease, except under the advice and supervision of a doctor
  - if you have trouble or pain swallowing food, vomiting with blood, or bloody or black stools. These may be signs of a serious condition. See your doctor.

- Ask a doctor before use if you have
  - nausea or vomiting
  - stomach pain
  - unexplained weight loss
  - frequent chest pain
  - frequent wheezing, particularly with heartburn
  - had heartburn over 3 months. This may be a sign of a more serious condition
  - heartburn with lightheadedness, sweating or dizziness
  - chest pain or shoulder pain with shortness of breath; sweating; pain spreading to arms, neck or shoulders; or lightheadedness
- Stop use and ask a doctor if
  - your heartburn continues or worsens
  - you need to take this product for more than 14 days
- If pregnant or breast feeding, ask a health professional before use.
- Keep out of reach of children. In case of overdose get medical help or contact a Poison Control Center right away.

Questions or Comments?

Call 1-800-706-5575 (Monday to Friday, 8:30 am – 5:00 pm Eastern Standard Time)

Manufactured by: Manufactured for:

Apotex Inc. Apotex Corp.

Toronto, Ontario Weston, FL

Canada M9L 1T9 33326

Repackaged By :
Aidarex Pharmaceuticals LLC,
Corona, CA 92880

Principal Display Panel

OTC Medicine

Maximum Strength

Rantidine Tablets USP, 150 mg